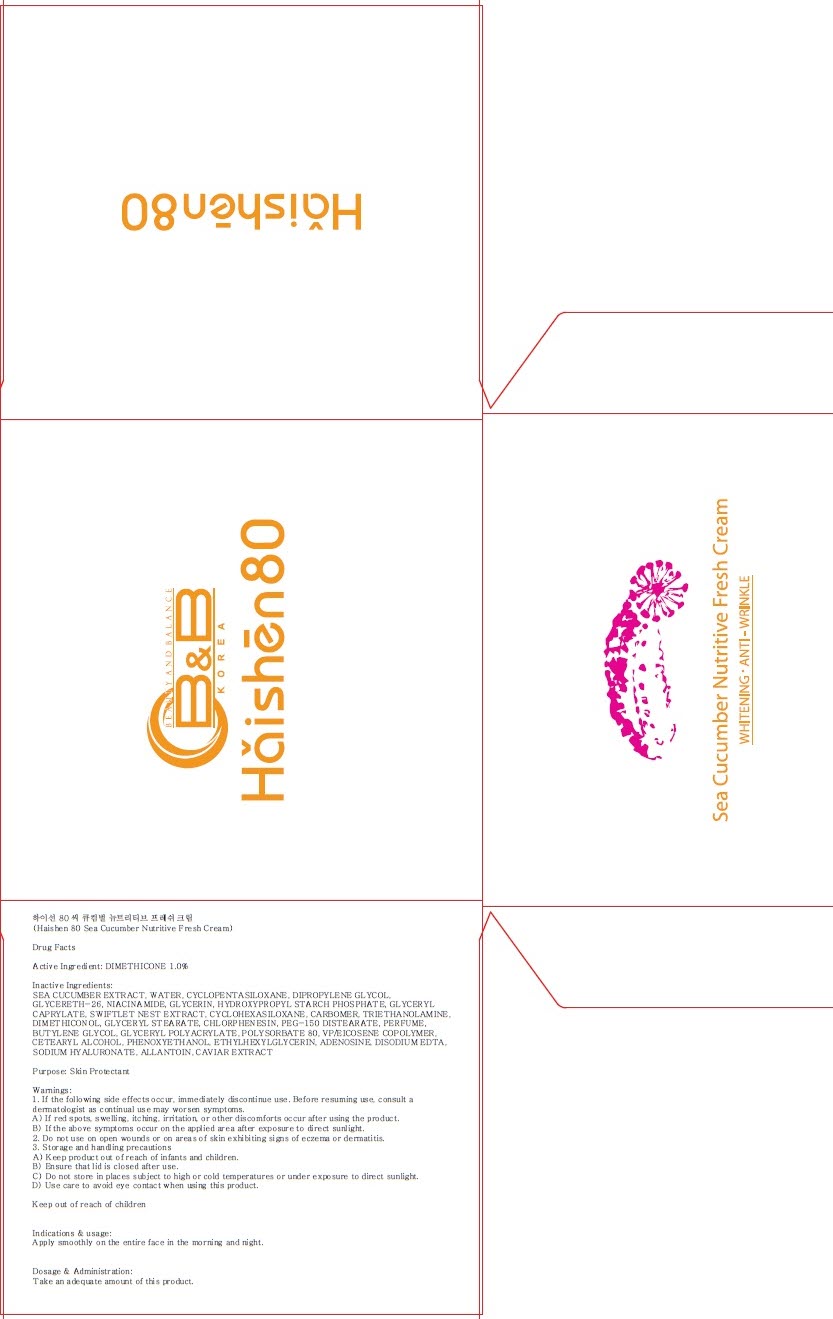 DRUG LABEL: Haishen 80 Sea Cucumber Nutritive Fresh
NDC: 70603-010 | Form: CREAM
Manufacturer: JUNGLEFOOD CO., LTD.
Category: otc | Type: HUMAN OTC DRUG LABEL
Date: 20160408

ACTIVE INGREDIENTS: DIMETHICONE 0.8 g/80 g
INACTIVE INGREDIENTS: WATER; NIACINAMIDE

ACTIVE INGREDIENT

Active Ingredient: DIMETHICONE 1.0%

INACTIVE INGREDIENT

Inactive Ingredients: SEA CUCUMBER EXTRACT, WATER, CYCLOPENTASILOXANE, DIPROPYLENE GLYCOL, GLYCERETH-26, NIACINAMIDE, GLYCERIN, HYDROXYPROPYL STARCH PHOSPHATE, GLYCERYL CAPRYLATE, SWIFTLET NEST EXTRACT, CYCLOHEXASILOXANE, CARBOMER, TRIETHANOLAMINE, DIMETHICONOL, GLYCERYL STEARATE, CHLORPHENESIN, PEG-150 DISTEARATE, PERFUME, BUTYLENE GLYCOL, GLYCERYL POLYACRYLATE, POLYSORBATE 80, VP/EICOSENE COPOLYMER, CETEARYL ALCOHOL, PHENOXYETHANOL, ETHYLHEXYLGLYCERIN, ADENOSINE, DISODIUM EDTA, SODIUM HYALURONATE, ALLANTOIN, CAVIAR EXTRACT

PURPOSE

Purpose: Skin Protectant

WARNINGS

Warnings: 1. If the following side effects occur, immediately discontinue use. Before resuming use, consult a dermatologist as continual use may worsen symptoms. A) If red spots, swelling, itching, irritation, or other discomforts occur after using the product. B) If the above symptoms occur on the applied area after exposure to direct sunlight. 2. Do not use on open wounds or on areas of skin exhibiting signs of eczema or dermatitis. 3. Storage and handling precautions A) Keep product out of reach of infants and children. B) Ensure that lid is closed after use. C) Do not store in places subject to high or cold temperatures or under exposure to direct sunlight. D) Use care to avoid eye contact when using this product.

KEEP OUT OF REACH OF CHILDREN

INDICATIONS & USAGE

Indications & usage: Apply smoothly on the entire face in the morning and night.

DOSAGE & ADMINISTRATION

Dosage & Administration: Take an adequate amount of this product.